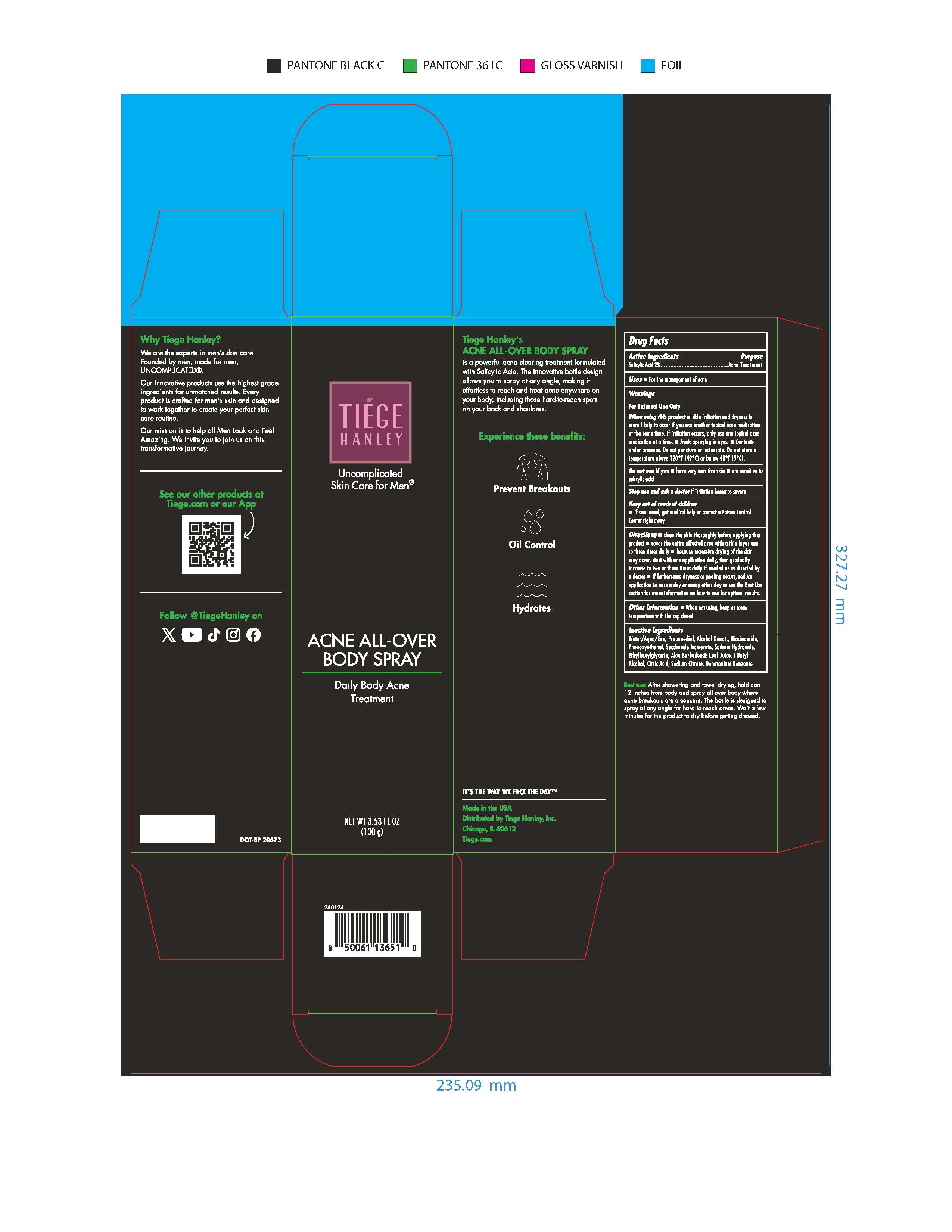 DRUG LABEL: Tiege Hanley Acne All Over Body
NDC: 71714-005 | Form: AEROSOL, SPRAY
Manufacturer: Tiege Hanley
Category: otc | Type: HUMAN OTC DRUG LABEL
Date: 20251223

ACTIVE INGREDIENTS: SALICYLIC ACID 2 g/100 g
INACTIVE INGREDIENTS: PROPANEDIOL; NIACINAMIDE; SODIUM HYDROXIDE; WATER; PHENOXYETHANOL; T-BUTYL ALCOHOL; ALCOHOL; ETHYLHEXYLGLYCERIN; SACCHARIDE ISOMERATE; CITRIC ACID; DENATONIUM BENZOATE; SODIUM CITRATE; ALOE BARBADENSIS LEAF JUICE

Acne All-Over Body Spray NDC 71714-005-01
Aerosol Can in an Outer Carton

Keep out of reach of children
■ if swallowed, get medical help or contact
a Poison Control Center right away

Directions

■ clean the skin thouroughly before applying this product

■ cover the entire affected area with a thin layer one to three times daily

■ because of excessive drying of the skin may occur, start with one application daily, then gradually increase to two times daily, then gradually increase to three times daily, if needed, or as directed by a doctor

■ if bothersome dryness or peeling occurs, reduce application to once a day or every other day

■ see the Best Use section for more information on how to use for optimal results.

Purpose.......Acne Treatment

ACTIVE INGREDIENT

Salicylic Acid 2%

Stop use and ask a doctor if irritation
becomes severe.

Inactive Ingredients:
Water/Aqua/Eau, Propanediol, Alcohol Denat, Niacinamide, Phenoxyethanol, Saccharide Isomerate, Sodium Hydroxide, Ethylhexylglycerin, Aloe Barbadensis Leaf Juice, t-Butyl Alcohol, Citric Acid, Sodium Citrate, Denatonium Benzoate

INDICATIONS AND USAGE

Uses ■ For the management of acne

Warnings
■ For External Use Only

When using this product ■ skin irritation
and dryness is more likely to occur if you
use another topical acne medication at the
same time. If irritation occurs, only use one
topical acne medication at a time.

■ Avoid spraying in eyes ■ Contents under pressure.

Do not puncture or incinerate. Do not store at a

temperature above 120°F11(49°C) or below 40°F11(5°C}.

Do not use if you ■ have very sensitive
skin ■ are sensitive to salicylic acid

Stop use and ask a doctor if irritation
becomes severe

Keep out of reach of children
■ if swallowed, get medical help or contact
a Poison Control Center right away